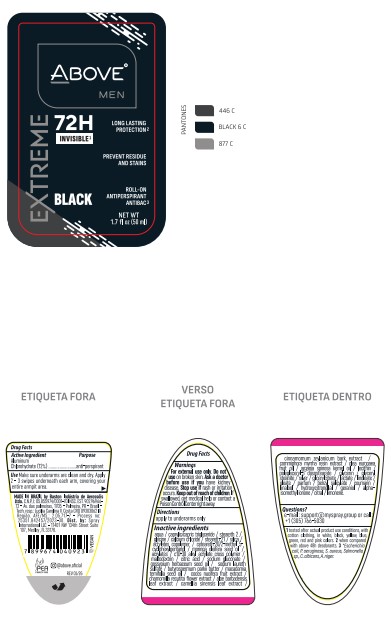 DRUG LABEL: ANTITRANSPIRANTE ABOVE ROLLON EXTREME BLACK
NDC: 73306-1183 | Form: CREAM
Manufacturer: BASTON INDUSTRIA DE AEROSSOIS LTDA
Category: otc | Type: HUMAN OTC DRUG LABEL
Date: 20260218

ACTIVE INGREDIENTS: ALUMINUM CHLOROHYDRATE ANHYDROUS 12 mg/50 mL
INACTIVE INGREDIENTS: ISOBUTANE

ANTITRANSPIRANTE ABOVE ROLLON EXTREME BLACK

ALUMINUM CHLOROHYDRATE 12%

ALUMINUM CHLOROHYDRATE ANTIPERSPIRANT

ALUMINUM CHLOROHYDRATE
ANTIPERSPIRANT

Use only on the armpits. Wait for it to dry before getting dressed. Do not apply to wet skin. Apply only to the underarms.

Use only on the armpits. Wait for it to dry before getting dressed. Do not apply to wet skin.
Apply only to the underarms.

SUPPORT@MYSPRAY.GROUP OR CALL (305) 766-5030

Use only in the indicated areas. Do not use if the skin is irritated or injured. If irritation and/or itching occurs at the application site, discontinue use immediately and seek medical advice. Keep out of reach of children and pets. Store in a dry place at room temperature with the cap closed. See packaging for batch number and expiry date.

KEEP OUT OF REACH OF CHILDREN

UNDERARM ANTIPERSPIRANT DEODORANT

Use only in the indicated areas. Do not use if the skin is irritated or injured. If irritation and/or itching occurs at the application site, discontinue use immediately and seek medical advice. Keep out of reach of children and pets. Store in a dry place at room temperature with the cap closed. See packaging for batch number and expiry date.

AQUA, ALUMINUM CHLOROHYDRATE, CAPRYLIC/CAPRIC TRIGLYCERIDE, STEARETH-2, GLYCINE, CALCIUM CHLORIDE, STEARETH-21, SILICA, ACRYLATES COPOLYMER, CETEARETH-20, 2-METHYL-5-CYCLOHEXYLPENTANOL, MORINGA OLEIFERA SEED OIL, ACRYLATES, C10-30 ALKYL ACRYLATE CROSSPOLYMER, MALTODEXTRIN, CITRIC ACID, SODIUM GLUCONATE, GOSSYPIUM HERBACEUM SEED OIL, SODIUM LAURETH SULFATE, BUTYROSPERMUM PARKII BUTTER, MACADAMIA TERNIFOLIA SEED OIL, COCOS NUCIFERA FRUIT EXTRACT, CHAMOMILLA RECUTITA FLOWER EXTRACT, ALOE BARBADENSIS LEAF EXTRACT, CAMELLIA SINENSIS LEAF EXTRACT, CINNAMOMUM ZEYLANICUM BARK EXTRACT, ACORUS CALAMUS ROOT EXTRACT, COMMIPHORA MYRRHA RESIN EXTRACT, OLEA EUROPAEA FRUIT OIL, ARGANIA SPINOSA KERNEL OIL, LECITHIN, POLYGLYCERYL-3 DIISOSTEARATE, GLYCERIN, GLYCERYL STEARATE, SILVER, GLYCERYL CITRATE/LACTATE/LINOLEATE/OLEATE, PARFUM, BENZYL SALICYLATE, COUMARIN, LINALOOL, HYDROXYCITRONELLAL, GERANIOL, ALPHA-ISOMETHYL IONONE, CITRAL, LIMONENE